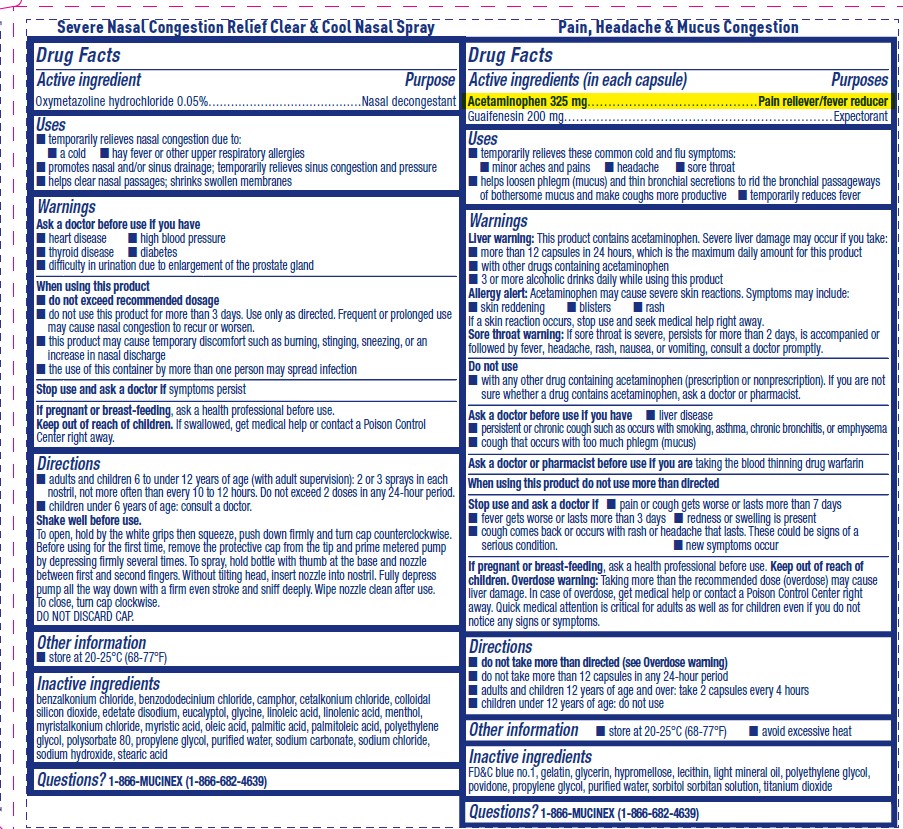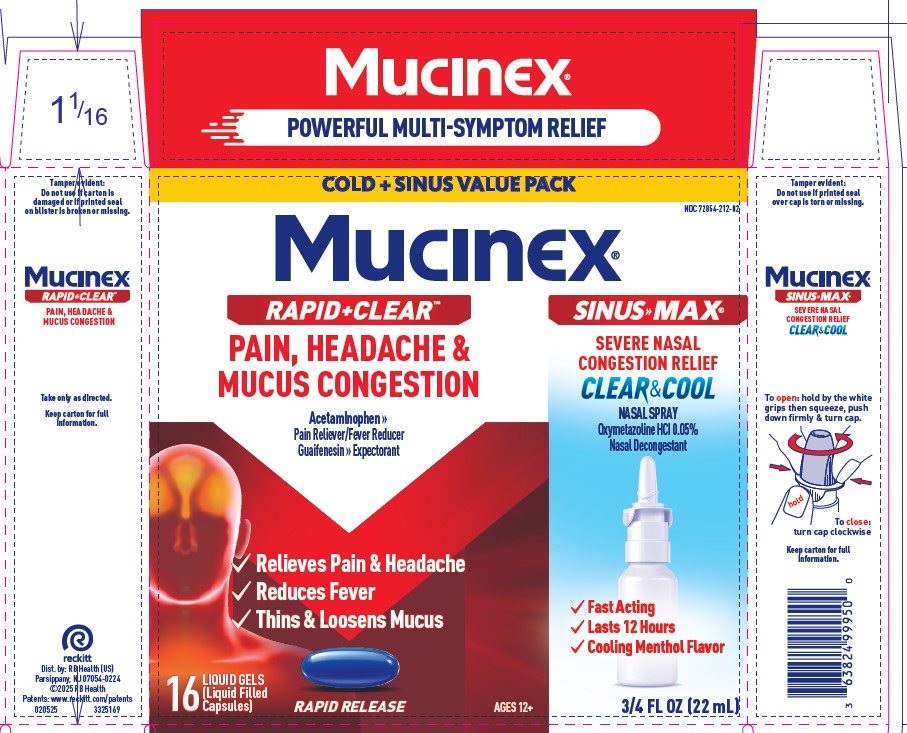 DRUG LABEL: Mucinex Rapid Clear Pain, Headache, and Mucus Congestion and Sinus Max Clear and Cool
NDC: 72854-212 | Form: KIT | Route: ORAL
Manufacturer: RB Health (US) LLC
Category: otc | Type: HUMAN OTC DRUG LABEL
Date: 20250610

ACTIVE INGREDIENTS: GUAIFENESIN 200 mg/1 1; ACETAMINOPHEN 325 mg/1 1; OXYMETAZOLINE HYDROCHLORIDE 0.05 g/100 mL
INACTIVE INGREDIENTS: GELATIN; GLYCERIN; HYPROMELLOSE, UNSPECIFIED; POLYETHYLENE GLYCOL, UNSPECIFIED; PROPYLENE GLYCOL; FD&C BLUE NO. 1; LECITHIN, SUNFLOWER; SORBITOL SOLUTION; LIGHT MINERAL OIL; TITANIUM DIOXIDE; POVIDONE; WATER; BENZALKONIUM CHLORIDE; BENZODODECINIUM CHLORIDE; CAMPHOR (NATURAL)

MUCINEX® RAPID+CLEAR Pain Headache & Mucus Congestion + MUCINEX® SINUS-MAX® Severe Nasal Congestion Relief CLEAR & COOL Nasal Spray

Active ingredient Purpose
Oxymetazoline hydrochloride 0.05%.........................................Nasal decongestant

Active ingredients (in each capsule) Purposes
Acetaminophen 325 mg.........................................Pain reliever/fever reducer
Guaifenesin 200 mg...................................................................Expectorant

Uses
■ temporarily relieves nasal congestion due to:
■ a cold ■ hay fever or other upper respiratory allergies
■ promotes nasal and/or sinus drainage; temporarily relieves sinus congestion and pressure
■ helps clear nasal passages; shrinks swollen membranes

Uses
■ temporarily relieves these common cold and flu symptoms:
■ minor aches and pains ■ headache ■ sore throat
■ helps loosen phlegm (mucus) and thin bronchial secretions to rid the bronchial passageways
of bothersome mucus and make coughs more productive ■ temporarily reduces fever

Warnings
Ask a doctor before use if you have
■ heart disease ■ high blood pressure
■ thyroid disease ■ diabetes
■ difficulty in urination due to enlargement of the prostate gland
When using this product
■ do not exceed recommended dosage
■ do not use this product for more than 3 days. Use only as directed. Frequent or prolonged use
may cause nasal congestion to recur or worsen.
■ this product may cause temporary discomfort such as burning, stinging, sneezing, or an
increase in nasal discharge
■ the use of this container by more than one person may spread infection

Warnings
Liver warning: This product contains acetaminophen. Severe liver damage may occur if you take:
■ more than 12 capsules in 24 hours, which is the maximum daily amount for this product
■ with other drugs containing acetaminophen
■ 3 or more alcoholic drinks daily while using this product
Allergy alert: Acetaminophen may cause severe skin reactions. Symptoms may include:
■ skin reddening ■ blisters ■ rash
If a skin reaction occurs, stop use and seek medical help right away.
Sore throat warning: If sore throat is severe, persists for more than 2 days, is accompanied or
followed by fever, headache, rash, nausea, or vomiting, consult a doctor promptly.
Do not use
■ with any other drug containing acetaminophen (prescription or nonprescription). If you are not
sure whether a drug contains acetaminophen, ask a doctor or pharmacist.

Directions
■ adults and children 6 to under 12 years of age (with adult supervision): 2 or 3 sprays in each
nostril, not more often than every 10 to 12 hours. Do not exceed 2 doses in any 24-hour period.
■ children under 6 years of age: consult a doctor.
Shake well before use.
To open, hold by the white grips then squeeze, push down firmly and turn cap counterclockwise.
Before using for the first time, remove the protective cap from the tip and prime metered pump
by depressing firmly several times. To spray, hold bottle with thumb at the base and nozzle
between first and second fingers.Without tilting head, insert nozzle into nostril. Fully depress
pump all the way down with a firm even stroke and sniff deeply.Wipe nozzle clean after use.
To close, turn cap clockwise.
DO NOT DISCARD CAP.

Directions
■ do not take more than directed (see Overdose warning)
■ do not take more than 12 capsules in any 24-hour period
■ adults and children 12 years of age and over: take 2 capsules every 4 hours
■ children under 12 years of age: do not use

Other information
■ store at 20-25°C (68-77°F)

■ avoid excessive heat

Inactive ingredients
benzalkonium chloride, benzododecinium chloride, camphor, cetalkonium chloride, colloidal
silicon dioxide, edetate disodium, eucalyptol, glycine, linoleic acid, linolenic acid, menthol,
myristalkonium chloride, myristic acid, oleic acid, palmitic acid, palmitoleic acid, polyethylene
glycol, polysorbate 80, propylene glycol, purified water, sodium carbonate, sodium chloride,
sodium hydroxide, stearic acid

Inactive ingredients
FD&C blue no.1, gelatin, glycerin, hypromellose, lecithin, light mineral oil, polyethylene glycol,
povidone, propylene glycol, purified water, sorbitol sorbitan solution, titanium dioxide

Keep out of reach of Children

Purpose

Oxymetazoline hydrochloride 0.05%.........................................Nasal decongestant

Acetaminophen 325 mg.........................................Pain reliever/fever reducer
Guaifenesin 200 mg...................................................................Expectorant